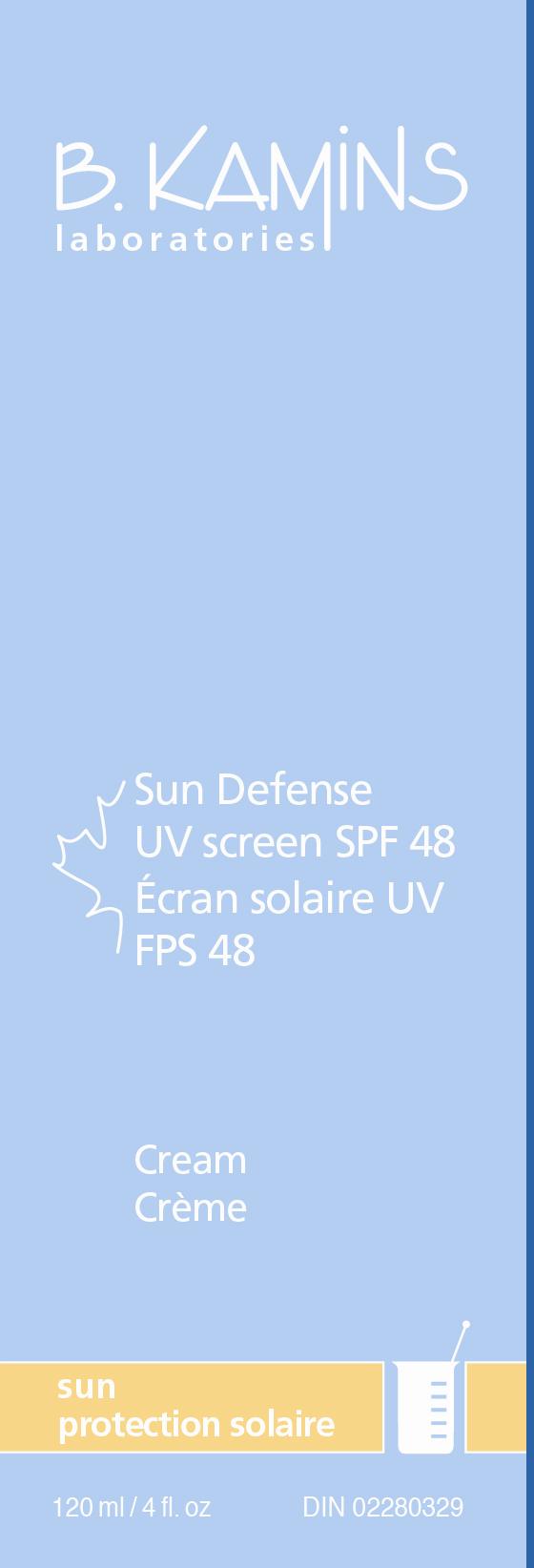 DRUG LABEL: Sun Defense UVscreen SPF 48
NDC: 63550-852 | Form: CREAM
Manufacturer: Kamins Dermatologics Inc.
Category: otc | Type: HUMAN OTC DRUG LABEL
Date: 20110902

ACTIVE INGREDIENTS: ENSULIZOLE 30 mg/1 mL; HOMOSALATE 100 mg/1 mL; OCTINOXATE 75 mg/1 mL; OCTOCRYLENE 70 mg/1 mL; ZINC OXIDE 80 mg/1 mL
INACTIVE INGREDIENTS: WATER; CYCLOMETHICONE 5; DIMETHICONE; ACER SACCHARUM SAP ; GLYCERIN; CYCLOMETHICONE 6; CETOSTEARYL ALCOHOL; STEARETH-100; C13-14 ISOPARAFFIN; LAURETH-7; STEARETH-2; LACTIC ACID; SODIUM HYDROXIDE; .ALPHA.-TOCOPHEROL ACETATE, D-; XANTHAN GUM; PHENOXYETHANOL; CHLORPHENESIN

SUN DEFENSE UVscreen SPF48 CONSUMER LABELING

Active ingredients:

Ensulizole 3%

Homosalate 10%

Octinoxate 7.5%

Octocrylene 7%

Zinc oxide 8%

Purpose: Sunscreen

Keep out of reach of children.

INDICATIONS AND USAGE

A hydrating, broad spectrum UVA/UVB sunscreen, which provides protection against sunburn. Combines our moisturizing Bio-MapleTM compound with a mixture of sunscreens that protect skin by scattering, reflecting and absorbing harmful sun rays. Fragrance, color and oil-free, ideal for those with sensitive skin.

Uses
■ Helps prevent sunburn.

■ Higher SPF gives more sunburn protection.

■ Provides high protection against sunburn.

Warnings
For external use only.
Avoid contact with eyes when using this product. If contact occurs, rinse abundantly with water to remove.
Discontinue use in case of excessive skin irritation or if condition does not improve. If irritation persists, consult a health care practitioner.
If swallowed, seek medical assistance or contact a Poison Control Center immediately.

Other information

Sun alert: Limiting sun exposure, wearing protective clothing, and using sunscreens may reduce the risks of skin aging, skin cancer, and other harmful effects of the sun.

Store at room temperature 15-30°C (59-86°F).

Directions
■ Apply liberally and evenly to face and exposed areas 15-30 minutes before sun exposure.

■ Reapply every two hours or as needed.

■ Reapply after swimming, towel drying, washing or perspiring heavily.

■ Consult a doctor before using on children under six months of age.

INACTIVE INGREDIENT

Inactive ingredients: water, cyclopentasiloxane, dimethiconol, acer saccharum (maple isolate), glycerin, cyclohexasiloxane, cetearyl alcohol, steareth-100, polyacrylamide, C13-14 isoparaffin, laureth-7, steareth-2, dimethicone, VP/eicosene copolymer, lactic acid, sodium hydroxide, dimethoxydiphenylsilane/triethoxycaprylylsilane crosspolymer, tocopheryl acetate, xanthan gum, phenoxyethanol, chlorphenesin.

PACKAGE LABEL

SUN DEFENSE UVscreen SPF 48
120 mL / 4 fl. oz
DIN 02280329
image/jpg